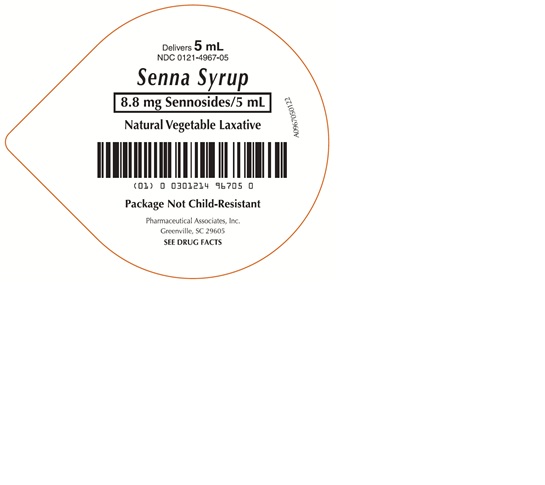 DRUG LABEL: Senna
NDC: 0121-4967 | Form: LIQUID
Manufacturer: PAI Holdings, LLC dba PAI Pharma
Category: otc | Type: HUMAN OTC DRUG LABEL
Date: 20250428

ACTIVE INGREDIENTS: SENNOSIDES 8.8 mg/5 mL
INACTIVE INGREDIENTS: CITRIC ACID ACETATE; GLYCERIN; METHYLPARABEN; POTASSIUM SORBATE; PROPYLPARABEN; WATER; SUCROSE

Senna

ACTIVE INGREDIENT

(per teaspoonful - 5 mL)

Sennosides - 8.8 mg

Purpose

Laxative

Uses

- relieves occasional constipation (irregularity)
- generally causes bowel movment in 6 to 12 hours

Warnings

Do not use

- laxative products for longer than 1 week unless directed by a doctor

Ask a doctor or pharmacist before use if you have

- stomach pain
- nausea
- vomiting
- noticed a sudden changed in bowel movement that continues over a period of 2 weeks

Stop use and ask a doctor if

you have rectal bleeding or failure to have a bowel movemebt after use of laxative. They may indicate a serious condition.

If pregnant or breast-feeding

ask a health professional before use.

Keep out of reach of children.

In case of accidental overdose, get medical help or contact a Poison Control Center (1-800-222-1222) immediately.

DOSAGE AND ADMINISTRATION

- shake well before use
- Do not exceed recommended dose

Age | Starting Dose | Maximum dosage
Adults and children 12 years and older | 2-3 teaspoonfuls once a day preferably at bedtime; increase as needed or as recommended by a doctor | 3 teaspoons in the morning and 3 teaspoons at bedtime
Under 12 years of age | ask a doctor | ask a doctor

Other information

- store at room temperature 20° to 25°C (68° to 77°F).
- a brown, natural flavored syrup supplied in the following oral dosage form:

NDC 0121-4967-05: 5 mL unit dose cup, in a tray of ten cups.
NDC 0121-4967-40: Case contains 40 unit dose cups of 5 mL (0121-4967-05) packaged in 4 trays of 10 unit dose cups each.

Inactive ingredients:

citric acid, glycerin, methylparaben, potassium sorbate, propylparaben, purified water, and sucrose.

Questions or comments?

1-800-845-8210

Distributed By:

Pharmaceutical Associates, Inc.

Greenville, SC 29605

Principal Display Panel

Delivers 5 mL
NDC 0121-4967-05

Senna Syrup

8.8 mg Sennosides/5 mL

Natural Vegetable Laxative

Package Not Child-Resistant

Pharmacutical Associates, Inc.
Greenville, SC 29605

SEE DRUG FACTS